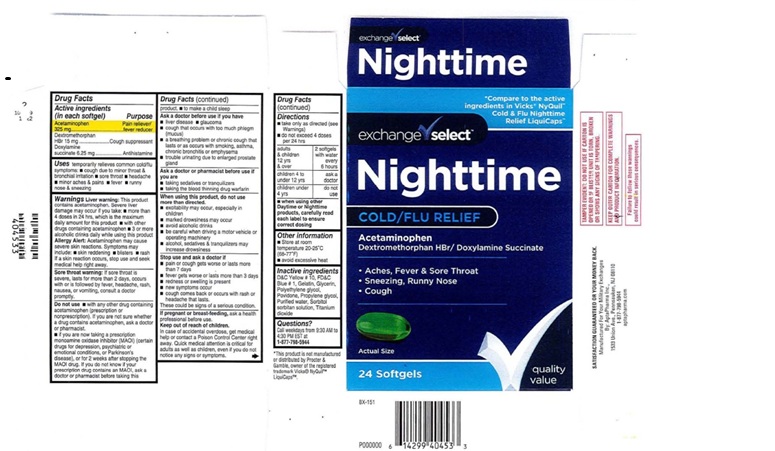 DRUG LABEL: Nighttime Cold/Flu Relief
NDC: 55301-603 | Form: CAPSULE, LIQUID FILLED
Manufacturer: ARMY AND AIR FORCE EXCHANGE SERVICE
Category: otc | Type: HUMAN OTC DRUG LABEL
Date: 20251219

ACTIVE INGREDIENTS: ACETAMINOPHEN 325 mg/1 1; DEXTROMETHORPHAN HYDROBROMIDE 15 mg/1 1; DOXYLAMINE SUCCINATE 6.25 mg/1 1
INACTIVE INGREDIENTS: D&C YELLOW NO. 10; FD&C BLUE NO. 1; GELATIN; GLYCERIN; POLYETHYLENE GLYCOL, UNSPECIFIED; POVIDONE; PROPYLENE GLYCOL; WATER; SORBITOL; SORBITAN; TITANIUM DIOXIDE

exchange select Nighttime Cold/Flu Relief

Drug Facts

Active ingredients
(in each Softgel)
Acetaminophen ................325 mg

Dextromethorphan HBr ......15 mg

Doxylamine succinate .........6.25 mg

Purpose

Acetaminophen ........................Pain reliever/Fever reducer

Dextromethorphan HBr .............Cough suppressant

Doxylamine succinate ............... Antihistamine

INDICATIONS AND USAGE

Usestemporarily relieves common cold/flu
symptoms: ■ cough due to minor throat &
bronchial irritation ■ sore throat ■ headache
■ minor aches and pain ■ fever ■ runny
nose and sneezing

WARNINGS

WarningsLiver warning : This product
contains acetaminophen. Severe liver
damage may occur if you take ■ more than
4doses in 24 hrs, which is the maximum
daily amount for this product ■ with other
drugs containing acetaminophen ■ 3 or more
alcoholic drinks daily while using this product.

Allergy Alert:Acetaminophen may cause
severe skin reactions. Symptoms may
include ■ skin reddening ■ blisters ■ rash.
If skin reaction occurs, stop use and seek
medical help right away.

Sore throat warning: If sore throat is
severe, lasts for more than 2 days, occurs
with or is followed by fever, headache, rash,
nausea or vomiting, consult a doctor
promptly.

Do not use: ■with any other products containing
Acetaminophen (prescription or
nonprescription). If you are not sure whether
a drug contains acetaminophen, ask a doctor
or pharmacist
■ if you are now taking a prescription
Monoamine oxidase inhibitor (MAOI) (certain
drugs for depression, psychiatric, or
emotional conditions, or Parkinson's
disease), or for 2 weeks after stopping the
MAOI drug. If you do not know if your
prescription drug contains an MAOI, ask
a doctor or pharmacist before taking this
product ■ to make a child sleep.

Ask a doctor before useif you have
■ liver disease ■ glaucoma
■ cough that occurs with too much phlegm
(mucus)
■ a breathing problem or chronic cough that
lasts or as occurs with smoking, asthma
chronic bronchitis or emphysema
■ trouble urinating due to an enlarged prostate
gland

Ask a doctor or pharmacistbefore use if you are
■ taking sedatives or tranquilizers
■ taking the blood thinning drug warfarin

When using this product, do not use
more than directed.
■ excitability may occur, especially in children,
■ marked drowsiness may occur
■ avoid alcoholic drinks
■ be careful when driving a motor vehicle or
operating machinery
■ alcohol, sedatives, and tranquilizers may
increase drowsiness

Stop use and ask a doctor if
■ pain or cough gets worse or lasts more
than 7 days
■ fever gets worse or lasts more than 3 days
■ redness or swelling
is present
■ new symptoms occur
■ cough comes back or occurs with rash or
headache that lasts.
These could be signs of a serious condition.

PREGNANCY OR BREAST FEEDING

If pregnant or breast-feeding, ask a health professional before use.

Keep out of reach of children.

In case of overdose, get medical help or contact a
Poison Control Center right away.

OVERDOSAGE

In case of accidental overdose, get medical
help or contact a Poison Control center right
away. Quick medical attention is critical for
adults as well as children even if you do not
notice any signs or symptoms.

Directions
■ take only as directed (see Warning)
■ do not exceed 4 doses per 24 hours

adults & children 12 yrs & over | 2 soft gels with water every 6 hours
children 4 to under 12 years: | ask a doctor
children under 4 years: | do not use

■ When using other
Daytime or Nighttime
products, carefully read
each label to ensure
correct dosing.

Other information
■ Store at room temperature 20-25º C (68-77º F)
■ avoid excessive heat

Inactive ingredients
D&C Yellow # 10, FD&C
Blue # 1, Gelatin, Glycerin,
Polyethylene glycol,
Povidone, Propylene glycol,
Purified water, Sorbitol
sorbitan solution, Titanium
dioxide.

QUESTIONS

Questions? Call Weekdays from 9:30 AM to 4:30 PM EST at
1-877-798-5944

Product Label: exchange select NightTime Cold/Flu Relief

exchange select

Nighttime

Cold/Flu Relief

24 Softgels

Manufactured For Your Military Exchange

By AptaPharma Inc.,

1533 Union Avenue, Pennsauken, NJ 08110

1-877-798-5944

aptapharma.com

res